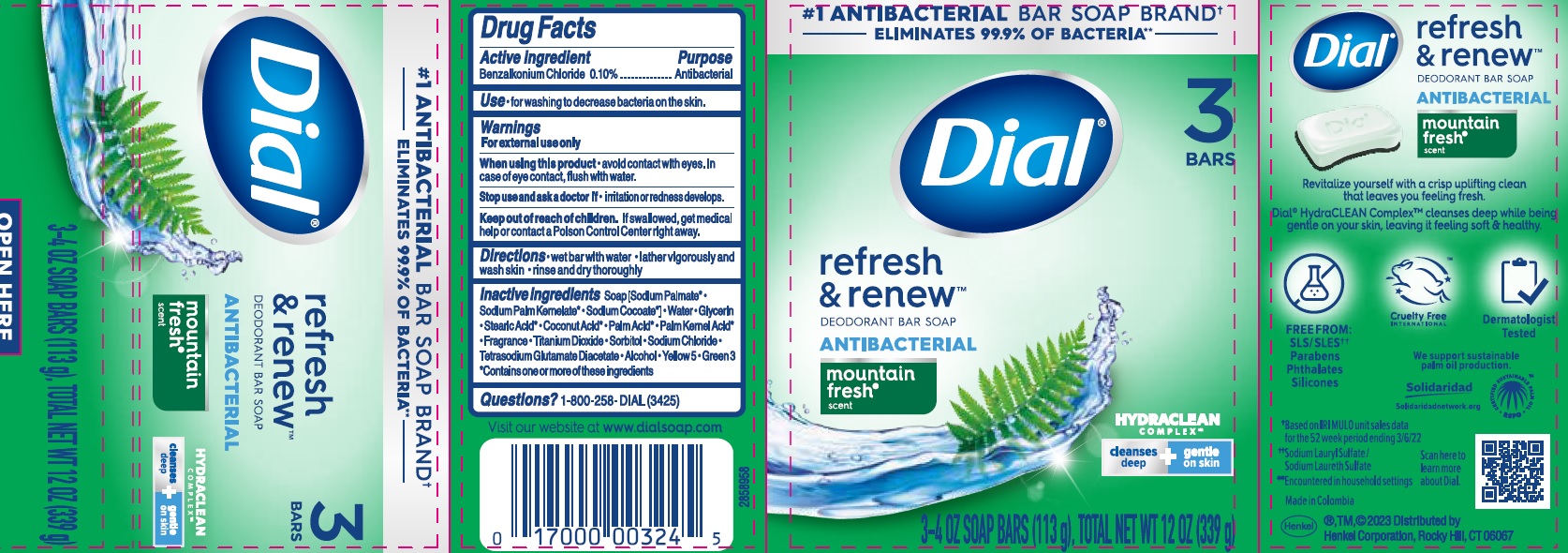 DRUG LABEL: Dial refresh and renew Antibacterial
NDC: 54340-017 | Form: SOAP
Manufacturer: Henkel Corporation
Category: otc | Type: HUMAN OTC DRUG LABEL
Date: 20241210

ACTIVE INGREDIENTS: BENZALKONIUM CHLORIDE 0.1 g/100 g
INACTIVE INGREDIENTS: SODIUM PALMATE; SODIUM PALM KERNELATE; SODIUM COCOATE; GLYCERIN; STEARIC ACID; COCONUT ACID; PALM ACID; PALM KERNEL ACID; SORBITOL; SODIUM CHLORIDE; ALCOHOL; TITANIUM DIOXIDE; FD&C GREEN NO. 3; WATER; TETRASODIUM GLUTAMATE DIACETATE; FD&C YELLOW NO. 5

Dial Mountain Fresh Antibacterial Soap

Active ingredient

Benzalkonium chloride 0.10%

Purpose

Antibacterial

Use

• for washing to decrease bacteria on the skin.

Warnings

For external use only

When using this product • avoid contact with eyes. In case of eye contact, flush with water.

Stop use and ask a doctor if • irritation or redness develops.

KEEP OUT OF REACH OF CHILDREN

Keep out of reach of chlidren. If swallowed, get medical help or contact a Poison Control Center right away.

Directions

• wet bar with water • lather vigorously and wash skin • rinse and dry thoroughly

Inactive ingredients

Soap [sodium palmate* • sodium palm kernelate* • sodium cocoate*] • water • glycerin • stearic acid* • coconut acid* • palm acid* • palm kernel acid* • fragrance • titanium dioxide • sortibol • sodium chloride • tetrasodium glutamate diacetate • alcohol • yellow 5 • green 3

*contains one or more of these ingredients

Questions?

1-800-258-DIAL (3425)

Dial® refresh & renew™

DEODORANT BAR SOAP

ANTIBACTERIAL

mountain fresh®

PACKAGE LABEL

®, TM, © 2023 Distributed by

Henkel Corporation, Rocky Hill, CT 06067

Made in Colombia

3-4 OZ SOAP BARS (113g), TOTAL NET WT 12 OZ (339g)